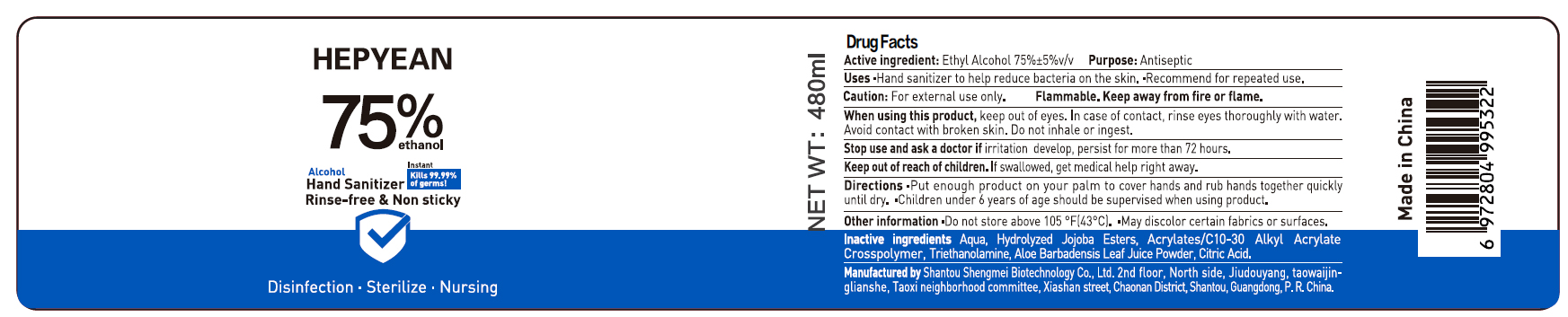 DRUG LABEL: Alcohol hand sanitizer
NDC: 55450-006 | Form: GEL
Manufacturer: Shantou Shengmei Biotechnology Co., Ltd.
Category: otc | Type: HUMAN OTC DRUG LABEL
Date: 20200417

ACTIVE INGREDIENTS: ALCOHOL 75 mL/100 mL
INACTIVE INGREDIENTS: CARBOMER INTERPOLYMER TYPE A (55000 CPS); HYDROLYZED JOJOBA ESTERS (ACID FORM); TROLAMINE; ALOE VERA LEAF; CITRIC ACID MONOHYDRATE; WATER

Alcohol hand sanitizer

ACTIVE INGREDIENT

Alcohol 75% v/v. Purpose: Antiseptic

PURPOSE

Antiseptic, Hand Sanitizer

INDICATIONS AND USAGE

Hand sanitizer to help reduce bacteria on the skin. Recommend for repeated use.

WARNINGS

For external use only.

Flammable. Keep away from heat or flame.

WHEN USING

Keep out of eyes. In case of contact with eyes, rinse eyes thoroughly with water. Avoid contact with broken skin. Do not inhale or ingest.

Stop use and ask a doctor if irritation develop, persisit for more than 72 hours.

keep out of reach of children. If sallowed, get medical help right away.

DOSAGE AND ADMINISTRATION

Place enough product on hands to cover hands and rub hands quickly until dry. Children under 6 years of age should be supervised when using product.

OTHER SAFETY INFORMATION

Do not store above 105F (43F). May discolor certain fabrics or surfaces.

INACTIVE INGREDIENT

Aqua, Hydrolyzed Jojoba Esters, Acrylates/C10-30 Alkyl Acrylate Crosspolymer, Triethanolamine, Aloe Barbadensis Leaf Juice Powder, Citric Acid

PACKAGE LABEL

55450-005-01 480mL